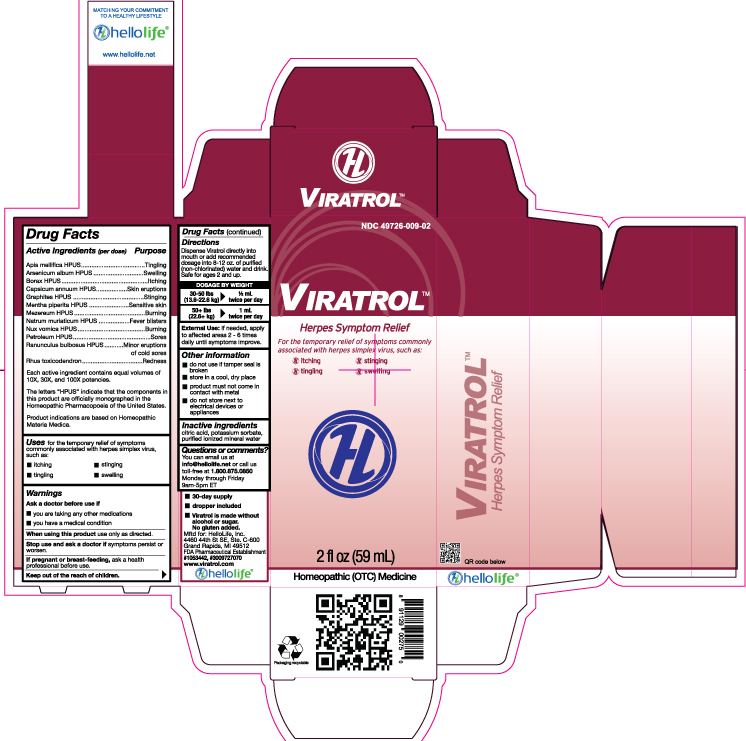 DRUG LABEL: Viratrol
NDC: 49726-009 | Form: LIQUID
Manufacturer: Hello Life, Inc.
Category: homeopathic | Type: HUMAN OTC DRUG LABEL
Date: 20181226

ACTIVE INGREDIENTS: APIS MELLIFERA 10 [hp_X]/59 mL; ARSENIC TRIOXIDE 10 [hp_X]/59 mL; SODIUM BORATE 10 [hp_X]/59 mL; CAPSICUM 10 [hp_X]/59 mL; GRAPHITE 10 [hp_X]/59 mL; PEPPERMINT 10 [hp_X]/59 mL; DAPHNE MEZEREUM BARK 10 [hp_X]/59 mL; SODIUM CHLORIDE 10 [hp_X]/59 mL; STRYCHNOS NUX-VOMICA SEED 10 [hp_X]/59 mL; PARAFFIN 10 [hp_X]/59 mL; RANUNCULUS BULBOSUS 10 [hp_X]/59 mL; TOXICODENDRON PUBESCENS LEAF 10 [hp_X]/59 mL
INACTIVE INGREDIENTS: WATER; POTASSIUM SORBATE; CITRIC ACID MONOHYDRATE

Drug Facts

Active Ingredients (per dose)

Apis mellifica
Arsenicum album
Borax
Capsicum annuum
Graphites
Mentha piperita
Mezereum
Natrum muriaticum
Nux vomica
Petroleum
Ranunculus bulbosus
Rhus toxicodendron

Each ingredient contains equal volumes of 10X, 30X and 100X potencies.
The letters “HPUS” indicate that the components in this product are officially monographed in the Homeopathic Pharmacopoeia of the United States.
Product indications are based on Homeopathic Materia Medica.

Purpose

Apis mellifica....................................Tingling
Arsenicum album ..............................Swelling
Borax.………………............................Itching
Capsicum annuum.............................Skin eruptions
Graphites..........................................Stinging
Mentha piperita............…..................Sensitive skin
Mezereum.........................................Burning
Natrum muriaticum....…………………..Fever blisters
Nux vomica……………………………..Burning
Petroleum..……………………….…….Sores
Ranunculus bulbosus.........………….Minor eruptions of cold sores
Rhus toxicodendron ….…………..….Redness

Uses

for temporary relief of symptoms commonly associated with herpes simplex virus such as:
• itching
• stinging
• tingling
• swelling

Warnings

Stop use and ask a doctor, if symptoms persist or worsen.

PREGNANCY OR BREAST FEEDING

If pregnant or breast-feeding, ask a health professional before use.

Keep out of the reach of children.

Directions

Dispense Viratrol directly into mouth, or add recommended dosage into 8-12 oz. of purified (non-chlorinated) water and drink. Safe for ages 2 and up.

DOSAGE BY WEIGHT

30-50 lbs 1/2 mL
(13.6-22.6 kg) twice per day
50+ lbs 1 mL
(22.6+ kg) twice per day

External Use: if needed, apply to affected areas 2-6 times daily until symptoms improve.

Other Information

- do not use if tamper seal is broken
- store in a cool, dry place
- product msut not come in contact with metal
- do not store next to electrical devices or appliance

Inactive Ingredients

citric acid, potassium sorbate, purified ionized mineral water

Questions or comments?

You can email us at info@hellolife.net or call us toll-free at 1.800.875.0850. Monday through Friday, 9am-5pm ET. www.hellolife.net

DESCRIPTION

- 30-day supply
- dropper included
- Viratrol is made without alcohol or sugar; no gluten added.

Mftd for: HelloLife, LLC 4460 44th St.
SE Ste. C-600 Grand Rapids, MI 49512
FDA Pharmaceutical Establishment
#1053442, #3009727070
www.viratrol.com

Principal Display Panel

NDC 49726-009-02

ViratrolTM

Herpes Symptom Relief

For the temporary relief of symptoms commonly associated with herpes simplex virus, such as:

- itching
- tingling
- stinging
- swelling

2 fl oz (59 mL)

Homeopathic (OTC) Medicine